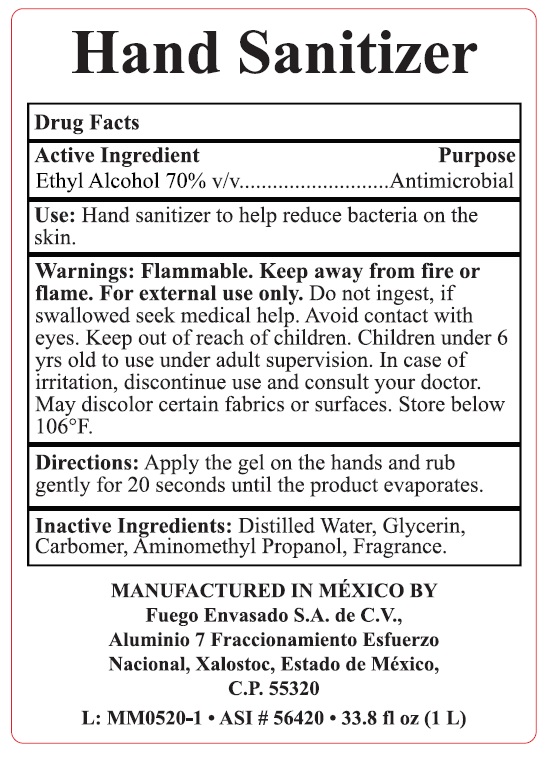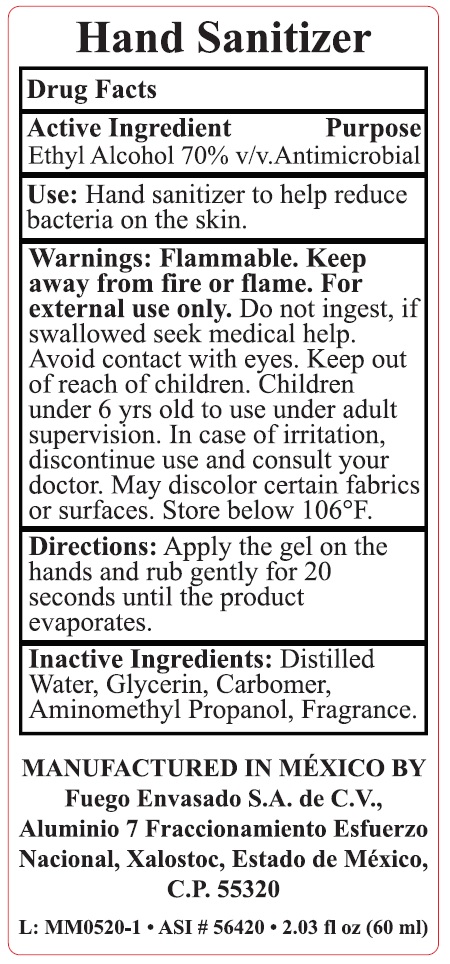 DRUG LABEL: HAND SANITIZER
NDC: 78325-001 | Form: GEL
Manufacturer: Laboratorios Descaa Mexico, S.A. de C.V
Category: otc | Type: HUMAN OTC DRUG LABEL
Date: 20200706

ACTIVE INGREDIENTS: ALCOHOL 70 mL/100 mL
INACTIVE INGREDIENTS: GLYCERIN; AMINOMETHYLPROPANOL; CARBOMER HOMOPOLYMER, UNSPECIFIED TYPE; WATER

HAND SANITIZER

Active Ingredient

Ethyl Alcohol 70%

Pupose

Antimicrobial

Warnings

For external use only. Flammable. Keep away from heat or flame

Do not ingest, if swallowed seek medical help. Avoid contact with eyes.

Keep out of reach of children.

Children under 6 years old to use under adult supervision. In case of irritation, discontinue use and consult your doctor.

May discolor certain fabrics or surfaces. Store below 106°F

Directions

Apply the gel on the hands and rub gently for 20 seconds until the product evaporates

Inactive Ingredients

Distilled Water, Glycerin, Carbomer, Aminomethyl propanol, Fragrance